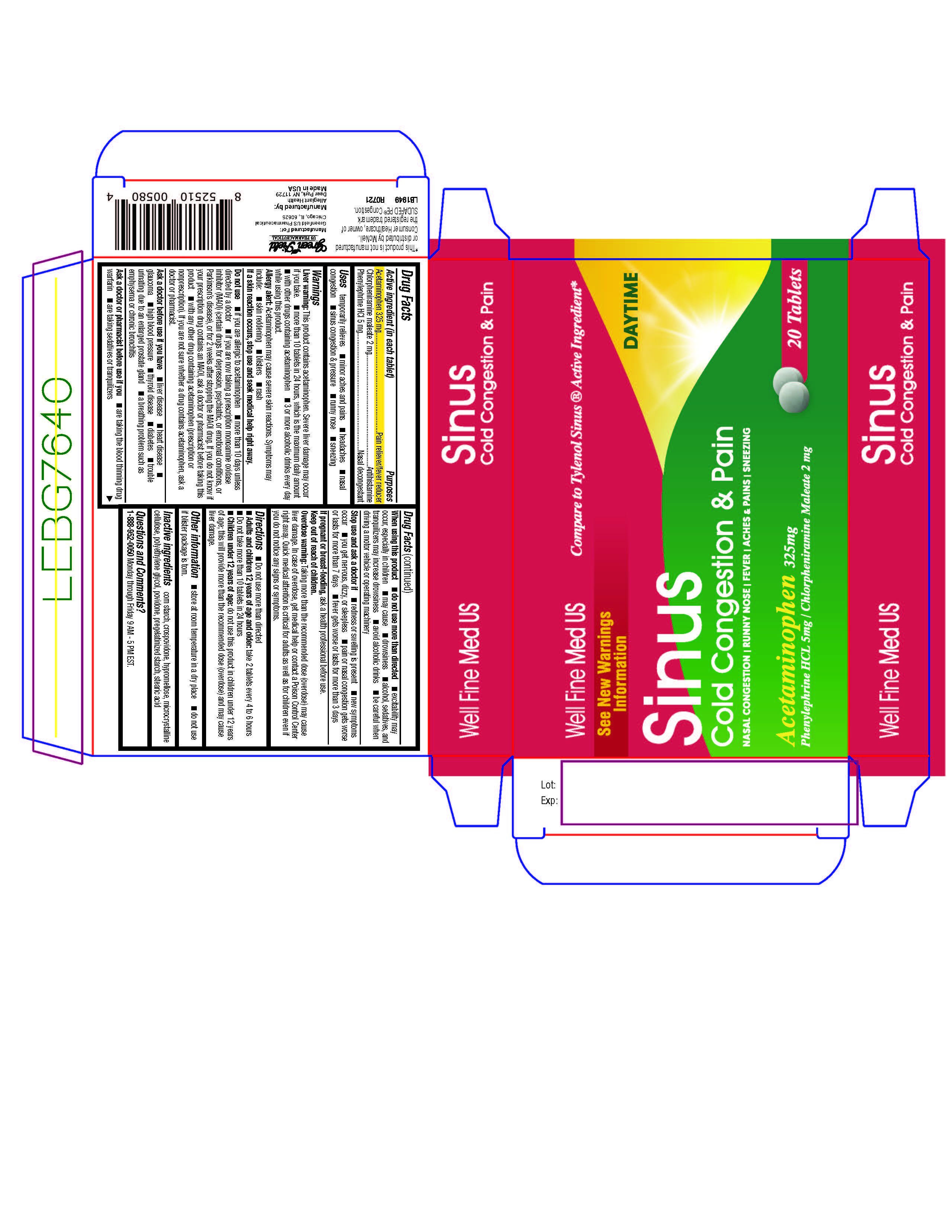 DRUG LABEL: Cold Medicine
NDC: 69168-004 | Form: TABLET
Manufacturer: Allegiant Health
Category: otc | Type: HUMAN OTC DRUG LABEL
Date: 20211123

ACTIVE INGREDIENTS: ACETAMINOPHEN 325 mg/1 1; CHLORPHENIRAMINE MALEATE 2 mg/1 1; PHENYLEPHRINE HYDROCHLORIDE 5 mg/1 1
INACTIVE INGREDIENTS: STARCH, CORN; CROSPOVIDONE; HYPROMELLOSE, UNSPECIFIED; MICROCRYSTALLINE CELLULOSE; POLYETHYLENE GLYCOL, UNSPECIFIED; POVIDONE; STEARIC ACID

GreenField - Cold Medicine

Active ingredient(s)

Acetaminophen 325 mg
Chlorpheniramine maleate 2 mg
Phenylephrine HCl 5 mg

Purpose

Pain reliever/fever reducer
Antihistamine
Nasal decongestant

Use(s)

temporarily relieves

- minor aches and pains
- headaches
- nasal congestion
- sinus congestion & pressure
- runny nose
- sneezing

Warnings

Liver warning: This product contains acetaminophen. Severe liver damage may occur if you take

- more than 10 tablets in 24 hours, which is the maximum daily amount
- with other drugs containing acetaminophen
- 3 or more alcoholic drinks every day while using this product.

Allergy alert: Acetaminophen may cause severe skin reactions. Symptoms may include:

- skin reddening
- blisters
- rash
  If a skin reaction occurs, stop use and seek medical help right away.

Do not use

- if you are allergic to acetaminophen

- more than 10 days unless directed by a doctor

- if you are now taking a prescription monoamine oxidase inhibitor (MAOI) (certain drugs for depression,

psychiatric, or emotional conditions, or Parkinson’s disease), or for 2 weeks after stopping the MAOI drug.

If you do not know if your prescription drug contains an MAOI, ask a doctor or pharmacist before taking this

product

- with any other drug containing acetaminophen (prescription or nonprescription). If you are not

sure whether a drug contains acetaminophen, ask a doctor or pharmacist.

Ask a doctor before use if

you have

- liver disease
- heart disease
- glaucoma
- high blood pressure
- thyroid disease
- diabetes
- trouble urinating due to an enlarged prostate gland
- a breathing problem such as emphysema or chronic bronchitis

Ask a doctor or pharmacist before use if

- are taking the blood thinning drug warfarin
- are taking sedatives or tranquilizers

When using this product

- do not use more than directed
- excitability may occur, especially in children
- may cause
- drowsiness
- alcohol, sedatives, and tranquilizers may increase drowsiness
- avoid alcoholic drinks
- be careful when driving a motor vehicle or operating machinery

Stop use and ask a doctor if

- redness or swelling is present
- new symptoms occur
- you get nervous, dizzy, or sleepless
- pain or nasal congestion gets worse or lasts for more than 7 days
- fever gets worse or lasts for more than 3 days

Pregnancy/Breastfeeding

If pregnant or breast-feeding, ask a health professional before use.

Keep out of reach of children

Overdose warning: Taking more than the recommended dose (overdose) may cause liver damage. In case of overdose, get medical
help or contact a Poison Control Center right away. Quick medical attention is critical for adults as well as for
children even if you do not notice any signs or symptoms.

Directions

- Do not use more than directed

- Adults and children 12 years of age and older: take 2 tablets every 4 to 6 hours
  Do not take more than 10 tablets in 24 hours

- Children under 12 years of age: do not use this product in children under 12 years
  of age; this will provide more than the recommended dose (overdose) and may cause
  liver damage.

Other information

- store at room temperature in a dry place
- do not use if blister package is torn.

Inactive ingredients

corn starch, crospovidone, hypromellose, microcrystalline
cellulose, polyethylene glycol, povidone, pregelatinized starch, stearic acid

Questions

1-888-952-0050 Monday through Friday 9 AM - 5 PM EST.

Principal Display Panel

Cold Congestion